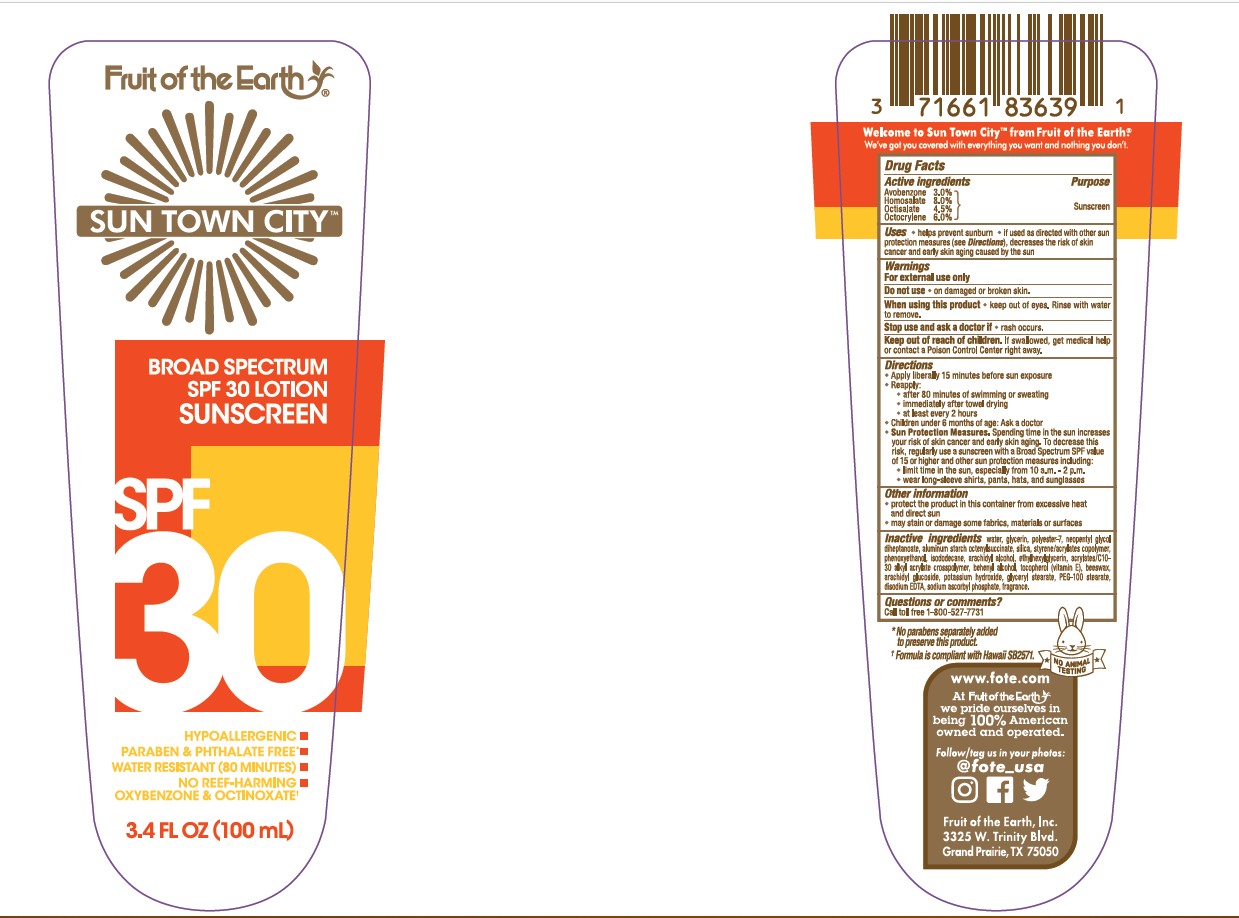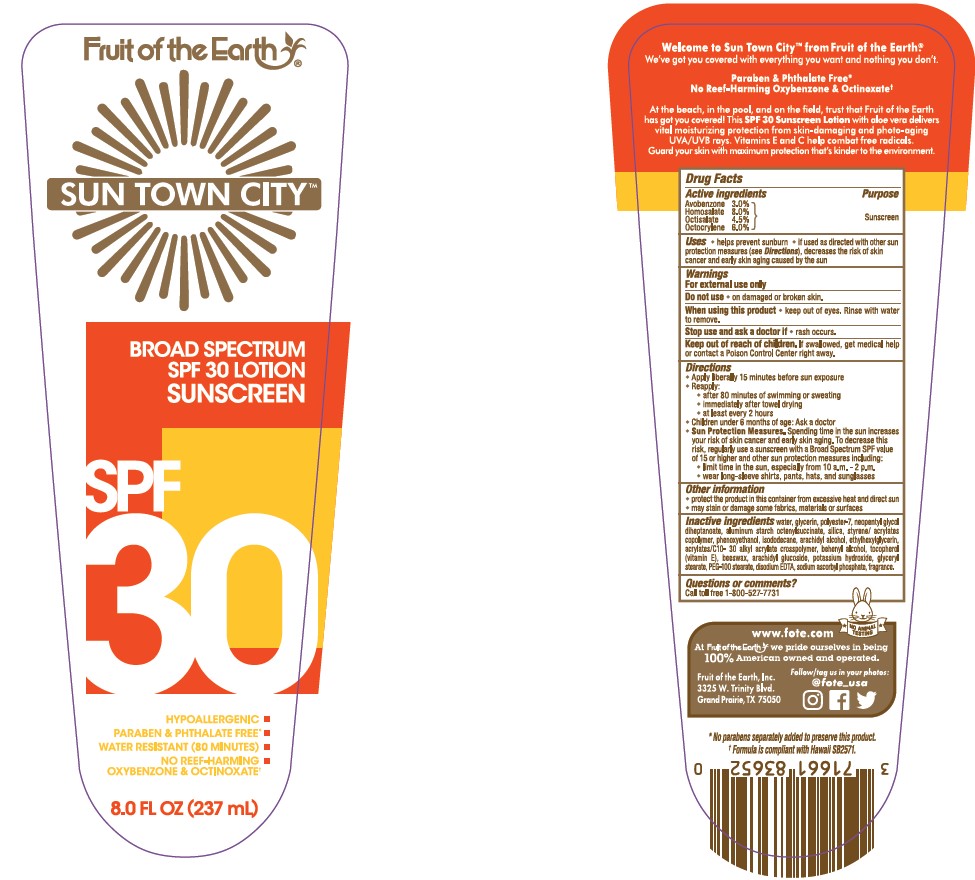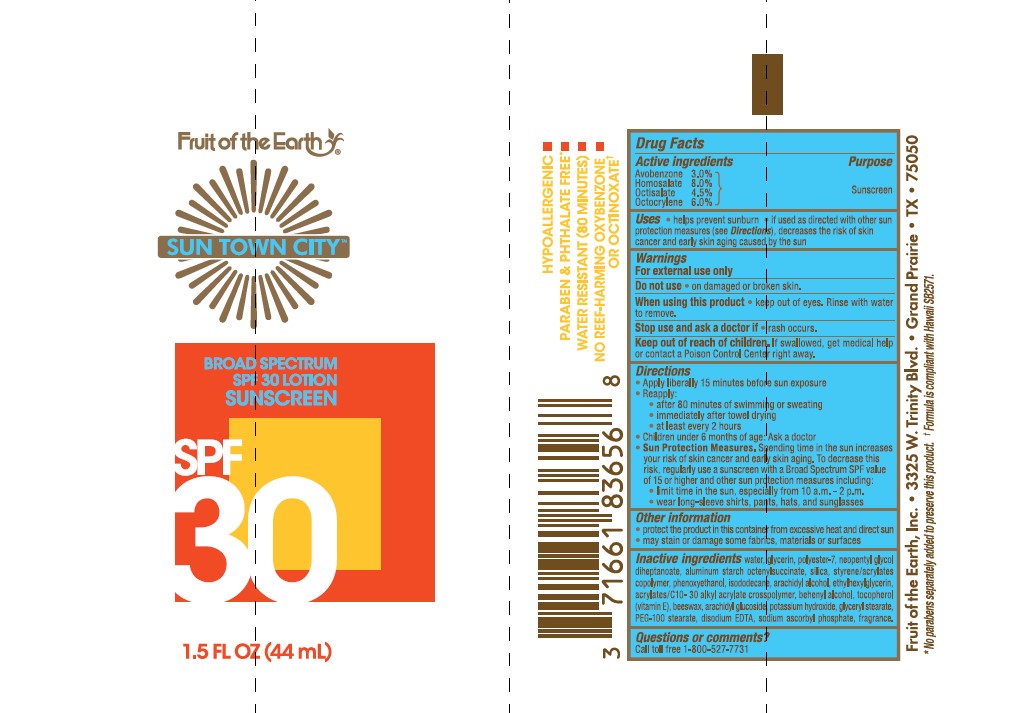 DRUG LABEL: Fruit of the Earth Sun Town City SPF 30 Sunscreen
NDC: 62217-079 | Form: LOTION
Manufacturer: Fruit of the Earth, Inc.
Category: otc | Type: HUMAN OTC DRUG LABEL
Date: 20241018

ACTIVE INGREDIENTS: AVOBENZONE 30 mg/1 mL; HOMOSALATE 80 mg/1 mL; OCTISALATE 45 mg/1 mL; OCTOCRYLENE 60 mg/1 mL
INACTIVE INGREDIENTS: BUTYL METHACRYLATE/METHYL METHACRYLATE/METHACRYLIC ACID/STYRENE CROSSPOLYMER; ARACHIDYL ALCOHOL; ETHYLHEXYLGLYCERIN; CARBOMER COPOLYMER TYPE A; DOCOSANOL; .ALPHA.-TOCOPHEROL, DL-; WHITE WAX; ARACHIDYL GLUCOSIDE; POTASSIUM HYDROXIDE; GLYCERYL 1-STEARATE; PEG-100 STEARATE; EDETATE DISODIUM; SODIUM ASCORBYL PHOSPHATE; WATER; GLYCERIN; POLYESTER-7; NEOPENTYL GLYCOL DIHEPTANOATE; ALUMINUM STARCH OCTENYLSUCCINATE; SILICON DIOXIDE; PHENOXYETHANOL; ISODODECANE

Fruit of the Earth Sun Town City SPF 30 Lotion Sunscreen

Active ingredients

Avobenzone 3.0%, Homosalate 8.0%, Octisalate 4.5%, Octocrylene 6.0%

Purpose

Sunscreen

Uses

• helps prevent sunburn • if used as directed with other sun protection measures (see Directions), decreases the risk of skin cancer and early skin aging casued by the sun

Warnings

For external use only

Do not use

• on damaged or broken skin.

When using this product

• keep out of eyes. Rinse with water to remove.

Stop use and ask a doctor if

• rash occurs.

Keep out of reach of children.

If swallowed, get medical help or contact a Poison Control Center right away.

Directions

- Apply liberally 15 minutes before sun exposure
- Reapply:

• after 80 minutes of swimming or sweating

• immediately after towel drying

• at least every 2 hours

- Children under 6 months of age: Ask a doctor
- Sun Protection Measures. Spending time in the sun increases your risk of skin cancer and early skin aging. To decrease this risk, regularly use a sunscreen with a Broad Spectrum SPF value of 15 or higher and other sun protection measures including:

• limit time in the sun, especially from 10 a.m.-2 p.m.

• wear long-sleeved shirts, pants, hats, and sunglasses

Other information

- protect the product in this container from excessive heat and direct sun
- may stain or damage some fabrics, materials or surfaces

Inactive ingredients

water, glycerin, polyester-7, neopentyl glycol diheptanoate, aluminum starch octenylsuccinate, silica, styrene/acrylates copolymer, phenoxyethanol, isododecane, arachidyl alcohol, ethylhexylglycerin, acrylates/C10-30 alkyl acrylate crosspolymer, behenyl alcohol, tocopherol (vitamin E), beeswax, arachidyl glucoside, potassium hydroxide, glyceryl stearate, PEG-100 stearate, disodium EDTA, sodium ascorbyl phosphate, fragrance.